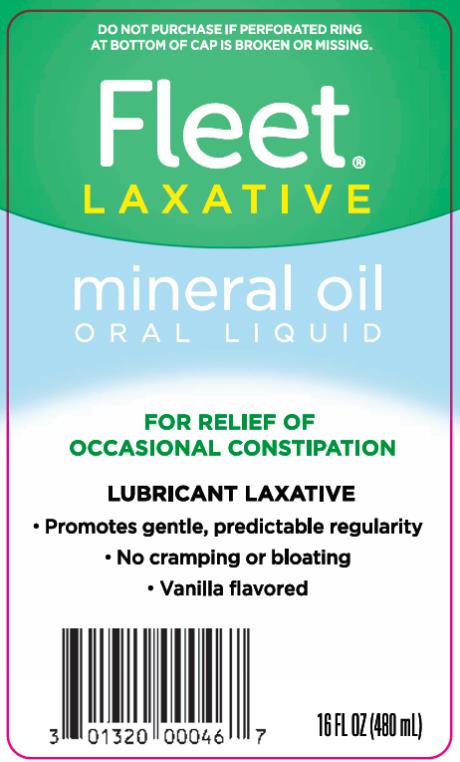 DRUG LABEL: FLEET
NDC: 0132-0400 | Form: LIQUID
Manufacturer: C.B. Fleet Company, Inc.
Category: otc | Type: HUMAN OTC DRUG LABEL
Date: 20240401

ACTIVE INGREDIENTS: MINERAL OIL 2.5 g/5 mL
INACTIVE INGREDIENTS: ACACIA; BENZOIC ACID; CARRAGEENAN; ETHYL VANILLIN; GLYCERIN; WATER; TITANIUM DIOXIDE; VANILLIN

Fleet Mineral Oil 0132-0400

Drug Facts

Active ingredient (in each 5 mL/teaspoonful)

Mineral Oil 2.5 mL.......................................

Purpose

Lubricant Laxative

Uses

▪ relieves occasional constipation

▪ generally produces bowel movement in 6 to 8 hours

Warnings

Do not use

▪ for children under 6 years of age, pregnant women, bedridden patients or persons with difficulty swallowing

Ask a doctor before using this product if you have

▪ abdominal pain, nausea or vomiting

▪ a sudden change in bowel habits that persists over a period of 2 weeks

Ask a doctor or pharmacist before use if you are

presently taking a stool softener laxative.

When using this product

do not take with meals.

Stop use and ask a doctor if

▪ you notice rectal bleeding or fail to have a bowel movement after use of a laxative. This may indicate a serious condition. Discontinue use and consult a doctor.

▪ you need to use the product more than one week

If breast-feeding,

ask a health professional before use.

Keep out of reach of children.

In case of overdose, get medical help or contact a Poison Control Center right away.

Directions

▪ do not take with meals

▪ shake well before using

▪ adults and children 12 years of age and over: 3 to 9 teaspoons (15 - 45 mL), maximum 9 teaspoons (45 mL) in 24 hours

▪ children 6 to under 12 years of age: 1 to 3 teaspoons (5 – 15 mL), maximum 3 teaspoons (15 mL) in 24 hours or as directed by a doctor

▪ children under 6 years of age: consult a doctor

Inactive ingredients

acacia, benzoic acid, carrageenan (irish moss), ethyl vanillin, glycerin, mapliene triple oil, purified water, titanium dioxide, vanillin

Other information

Store at room temperature 15°-25°C (59°-77°F)

Questions?

Call toll-free 1-855-727-4277

Principal Display Panel

Fleet ®
Laxative
Mineral Oil
Oral Liquid
Lubricant Laxative

16 FL OZ (480 mL)